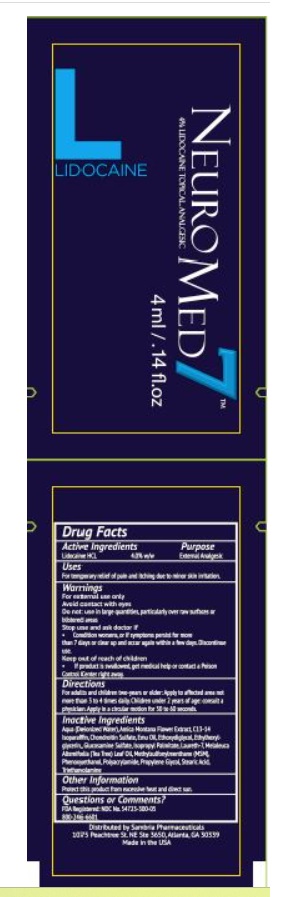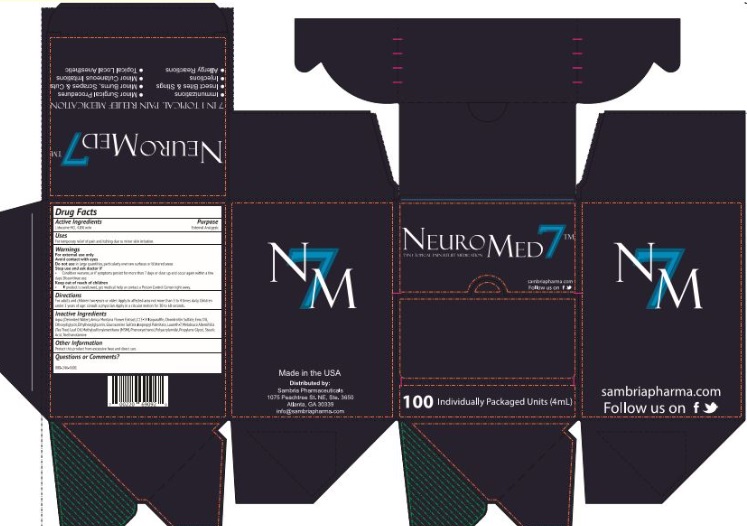 DRUG LABEL: NeuroMed Topical Anesthetic


NDC: 54723-300 | Form: CREAM
Manufacturer: Sambria Pharmaceuticals
Category: otc | Type: HUMAN OTC DRUG LABEL
Date: 20251112

ACTIVE INGREDIENTS: LIDOCAINE HYDROCHLORIDE 40 mg/1 g
INACTIVE INGREDIENTS: WATER; ARNICA MONTANA FLOWER; C13-14 ISOPARAFFIN; SODIUM CHONDROITIN SULFATE (PORCINE; 5500 MW); EMU OIL; DIETHYLENE GLYCOL MONOETHYL ETHER; ETHYLHEXYLGLYCERIN; GLUCOSAMINE SULFATE; ISOPROPYL PALMITATE; LAURETH-7; MELALEUCA ALTERNIFOLIA LEAF; DIMETHYL SULFONE; PHENOXYETHANOL; POLYACRYLAMIDE (10000 MW); PROPYLENE GLYCOL; STEARIC ACID; TROLAMINE

NeuroMed 7 Topical Anesthetic

Active Ingredient

Lidocaine HCL 4.00% w/w

Purpose

External Analgesic

Uses

For temporary relief of pain and itching due to minor skin irritation.

Warnings

For external use only

Avoid contact with eyes

Do not use in large quantities, particularly over raw surfaces or blistered areas

Stop use and ask a doctor if

• Condition worsens, or if symptoms persist for more than 7 days or clear up and occur again within a few days. Discontinue use.

Keep out of reach of children

• If product is swallowed, get medical help or contact a Poison Control Center right away.

Directions

For adults and children two-years or older: Apply to affected area not more than 3 or 4 times daily. Children under 2 years of age: consult a physician. Apply in a circular motion for 50 to 60 seconds.

Inactive Ingredients

Aqua (Deionized Water), Arnica Montana Flower Extract, C13-14 Isoparaffin, Chrondroitin Sulfate, Emu Oil, Ethoxydiglycol, Ethylhexyglycerin, Glucosamine Sulfate, Isopropyl Palmitate, Laureth-7, Melaleuca Alternifolia (Tea Tree) Oil, Methylsulfonylmethane (MSM), Phenoxyethanol, Polyacrylamide, Propylene Glycol, Stearic Acid, Triethanolamine.

Other Information

Protect this product from excessive heat and direct sun.

Questions or Comments?

FDA Registered: NDC No. 54723-667-04

800-759-6876